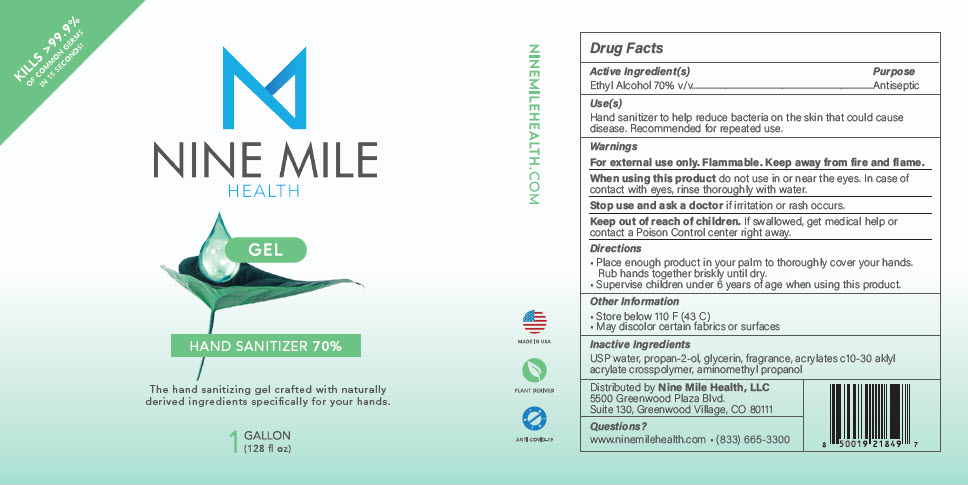 DRUG LABEL: HAND SANITIZER
NDC: 78697-070 | Form: GEL
Manufacturer: Nine Mile Health, LLC
Category: otc | Type: HUMAN OTC DRUG LABEL
Date: 20200904

ACTIVE INGREDIENTS: ALCOHOL 70 mL/100 mL
INACTIVE INGREDIENTS: WATER; GLYCERIN; CARBOMER INTERPOLYMER TYPE A (ALLYL SUCROSE CROSSLINKED); AMINOMETHYLPROPANOL

HAND SANITIZER

Drug Facts

Active Ingredient(s)

Ethyl Alcohol 70% v/v

Purpose

Antiseptic

Use(s)

Hand sanitizer to help reduce bacteria on the skin that could cause disease. Recommended for repeated use.

Warnings

For external use only. Flammable. Keep away from fire and flame.

When using this product do not use in or near the eyes. In case of contact with eyes, rinse thoroughly with water.

Stop use and ask a doctor if irritation or rash occurs.

Keep out of reach of children. If swallowed, get medical help or contact a Poison Control center right away.

Directions

- Place enough product in your palm to thoroughly cover your hands. Rub hands together briskly until dry.
- Supervise children under 6 years of age when using this product.

Other Information

- Store below 110 F (43 C)
- May discolor certain fabrics or surfaces

Inactive Ingredients

USP water, propan-2-ol, glycerin, fragrance, acrylates c10-30 aklyl acrylate crosspolymer, aminomethyl propanol

Distributed by Nine Mile Health, LLC
5500 Greenwood Plaza Blvd.
Suite 130, Greenwood Village, CO 80111

Questions?

www.ninemilehealth.com ▪ (833) 665-3300

PRINCIPAL DISPLAY PANEL - 128 fl oz Bottle Label

KILLS >99.9%
OF COMMON GERMS
IN 15 SECONDS!

NINE MILE
HEALTH

GEL

HAND SANITIZER 70%

The hand sanitizing gel crafted with naturally
derived ingredients specifically for your hands.

1 GALLON
(128 fl oz)